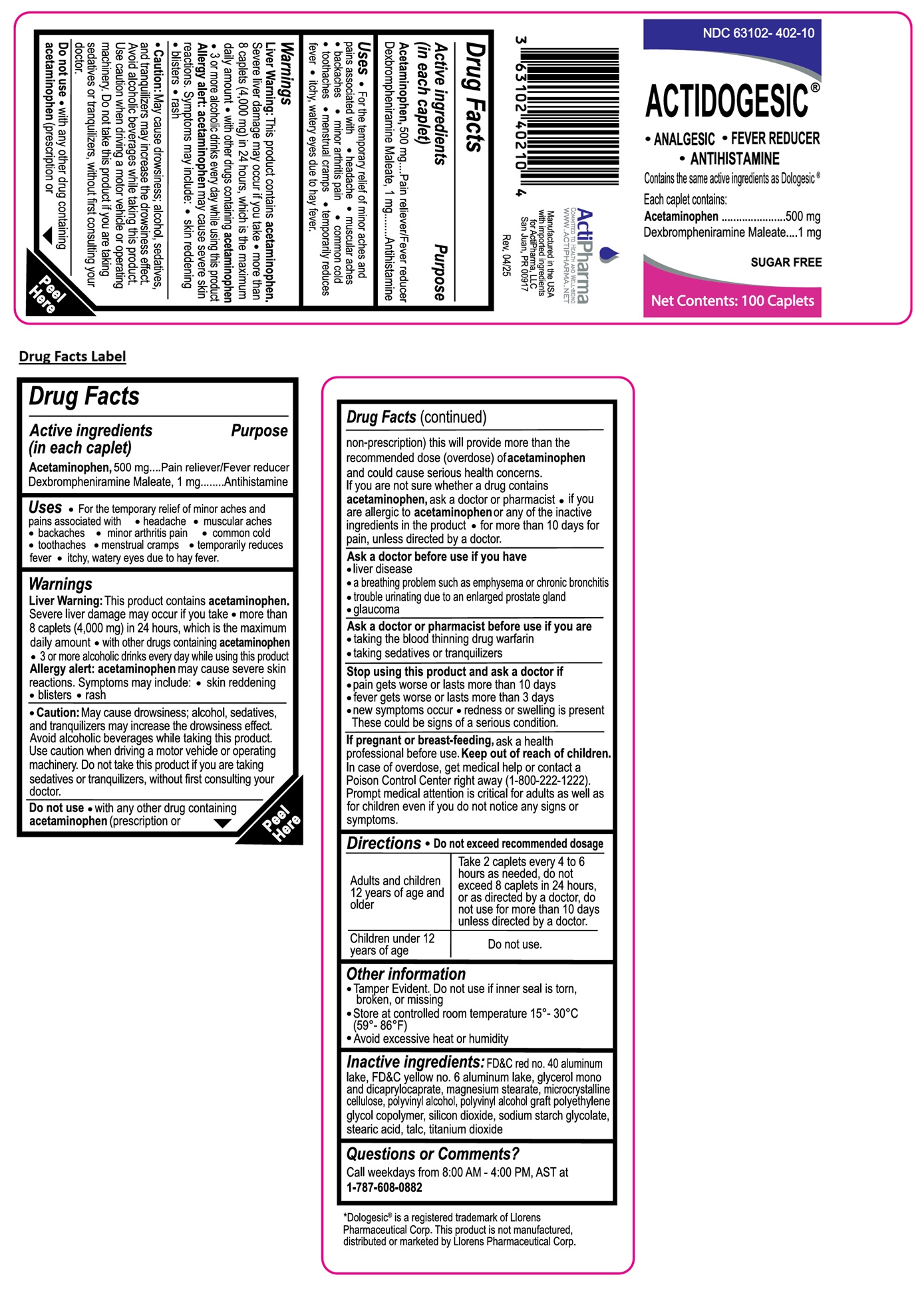 DRUG LABEL: ACTIDOGESIC
NDC: 63102-402 | Form: TABLET
Manufacturer: ACTIPHARMA, LLC
Category: otc | Type: HUMAN OTC DRUG LABEL
Date: 20250818

ACTIVE INGREDIENTS: DEXBROMPHENIRAMINE MALEATE 1 mg/1 1; ACETAMINOPHEN 500 mg/1 1
INACTIVE INGREDIENTS: FD&C RED NO. 40 ALUMINUM LAKE; FD&C YELLOW NO. 6 ALUMINUM LAKE; GLYCERYL MONO- AND DICAPRYLOCAPRATE; MAGNESIUM STEARATE; MICROCRYSTALLINE CELLULOSE; POLYVINYL ALCOHOL, UNSPECIFIED; POLYVINYL ALCOHOL GRAFT POLYETHYLENE GLYCOL COPOLYMER (3:1; 45000 MW); SILICON DIOXIDE; SODIUM STARCH GLYCOLATE TYPE A; STEARIC ACID; TALC; TITANIUM DIOXIDE

ACTIDOGESIC®

Active ingredients (in each caplet)

Acetaminophen, 500 mg
Dexbrompheniramine Maleate, 1 mg

Purpose

Pain reliever/Fever reducer
Antihistamine

Uses

• For the temporary relief of minor aches and pains associated with • headache • muscular aches • backaches • minor arthritis pain • common cold • toothaches • menstrual cramps • temporarily reduces fever • itchy, watery eyes due to hay fever.

Warnings

Liver Warning: This product contains acetaminophen. Severe liver damage may occur if you take • more than 8 caplets (4,000 mg) in 24 hours, which is the maximum daily amount • with other drugs containing acetaminophen • 3 or more alcoholic drinks every day while using this product
Allergy alert: acetaminophen may cause severe skin reactions. Symptoms may include: • skin reddening • blisters • rash

• Caution: May cause drowsiness; alcohol, sedatives, and tranquilizers may increase the drowsiness effect. Avoid alcoholic beverages while taking this product. Use caution when driving a motor vehicle or operating machinery. Do not take this product if you are taking sedatives or tranquilizers, without first consulting your doctor.

Do not use • with any other drug containing acetaminophen (prescription or non-prescription) this will provide more than the recommended dose (overdose) of acetaminophen and could cause serious health concerns.
If you are not sure whether a drug contains acetaminophen, ask a doctor or pharmacist • if you are allergic to acetaminophen or any of the inactive ingredients in the product • for more than 10 days for pain, unless directed by a doctor.

Ask a doctor before use if you have
• liver disease
• a breathing problem such as emphysema or chronic bronchitis
• trouble urinating due to an enlarged prostate gland
• glaucoma

Ask a doctor or pharmacist before use if you are
• taking the blood thinning drug warfarin
• taking sedatives or tranquilizers

Stop using this product and ask a doctor if
• pain gets worse or lasts more than 10 days
• fever gets worse or lasts more than 3 days
• new symptoms occur • redness or swelling is present
These could be signs of a serious condition.

If pregnant or breast-feeding, ask a health professional before use.

Keep out of reach of children. In case of overdose, get medical help or contact a Poison Control Center right away (1-800-222-1222). Prompt medical attention is critical for adults as well as for children even if you do not notice any signs or symptoms.

Directions

• Do not exceed recommended dosage

Adults and children 12 years of age and older | Take 2 caplets every 4 to 6 hours as needed, do not exceed 8 caplets in 24 hours, or as directed by a doctor, do not use for more than 10 days unless directed by a doctor.
Children under 12 years of age | Do not use.

Other information

• Tamper Evident. Do not use if inner seal is torn, broken, or missing
• Store at controlled room temperature 15°-30°C (59°-86°F)
• Avoid excessive heat or humidity

Inactive ingredients:

FD&C red no. 40 aluminum lake, FD&C yellow no. 6 aluminum lake, glycerol mono and dicaprylocaprate, magnesium stearate, microcrystalline cellulose, polyvinyl alcohol, polyvinyl alcohol graft polyethylene glycol copolymer, silicon dioxide, sodium starch glycolate, stearic acid, talc, titanium dioxide

Questions or Comments?

Call weekdays from 8:00 AM - 4:00 PM, AST at 1-787-608-0882

• ANALGESIC • FEVER REDUCER • ANTIHISTAMINE

Contains the same active ingredients as Dologesic®

SUGAR FREE

ActiPharma
COMMITTED TO HEALTH AND WELL-BEING
WWW.ACTIPHARMA.NET

Manufactured in the USA with imported ingredients for ActiPharma, LLC San Juan, PR 00917

*Dologesic® is a registered trademark of Llorens Pharmaceutical Corp. This product is not manufactured, distributed or marketed by Llorens Pharmaceutical Corp.